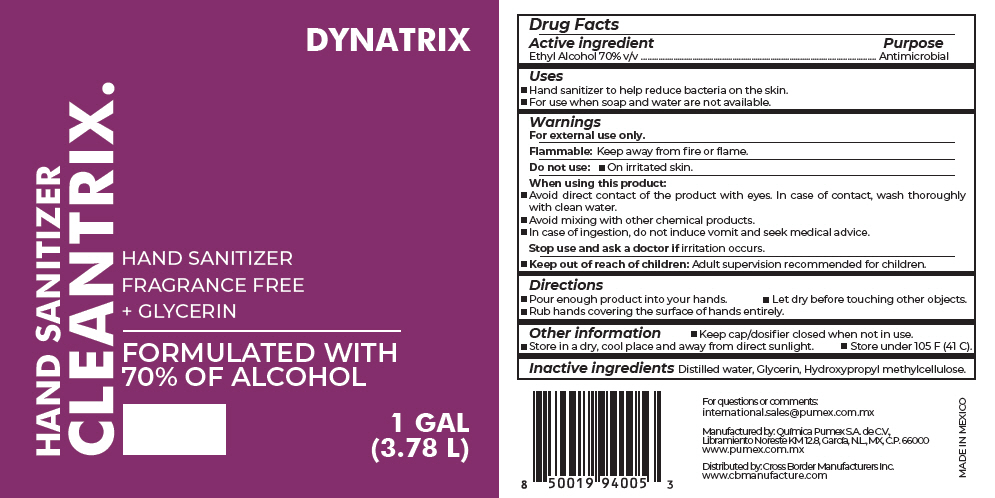 DRUG LABEL: HAND SANITIZER
NDC: 79072-004 | Form: LIQUID
Manufacturer: Química Pumex SA de CV
Category: otc | Type: HUMAN OTC DRUG LABEL
Date: 20200803

ACTIVE INGREDIENTS: alcohol 0.07 L/0.1 L
INACTIVE INGREDIENTS: water; Glycerin; HYPROMELLOSE, UNSPECIFIED

HAND SANITIZER

Drug Facts

Active ingredient

Ethyl Alcohol 70% v/v

Purpose

Antimicrobial

Uses

- Hand sanitizer to help reduce bacteria on the skin.
- For use when soap and water are not available.

Warnings

For external use only.

Flammable: Keep away from fire or flame.

Do not use

- On irritated skin.

When using this product

- Avoid direct contact of the product with eyes. In case of contact, wash thoroughly with clean water.
- Avoid mixing with other chemical products.
- In case of ingestion, do not induce vomit and seek medical advice.

Stop use and ask a doctor if irritation occurs.

- Keep out of reach of children: Adult supervision recommended for children.

Directions

- Pour enough product into your hands.
- Let dry before touching other objects.
- Rub hands covering the surface of hands entirely.

Other information

- Keep cap/dosifier closed when not in use.
- Store in a dry, cool place and away from direct sunlight.
- Store under 105 F (41 C).

Inactive ingredients

Distilled water, Glycerin, Hydroxypropyl methylcellulose.

For questions or comments:
international.sales@pumex.com.mx

Manufactured by: Química Pumex S.A. de C.V.,
Libramiento Noreste KM 12.8, García, N.L., MX, C.P. 66000

Distributed by: Cross Border Manufacturers Inc.

PRINCIPAL DISPLAY PANEL - 3.78 L Bottle Label

DYNATRIX

HAND SANITIZER
CLEANTRIX.

HAND SANITIZER
FRAGRANCE FREE
+ GLYCERIN

FORMULATED WITH
70% OF ALCOHOL

1 GAL
(3.78 L)